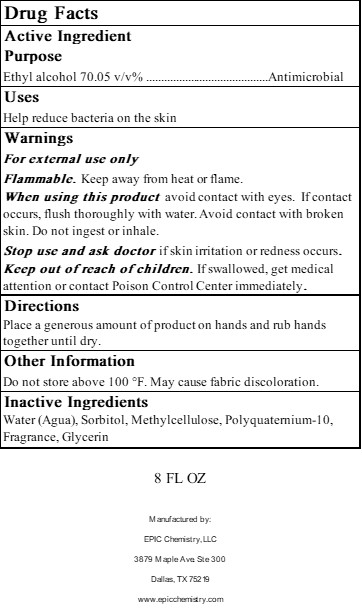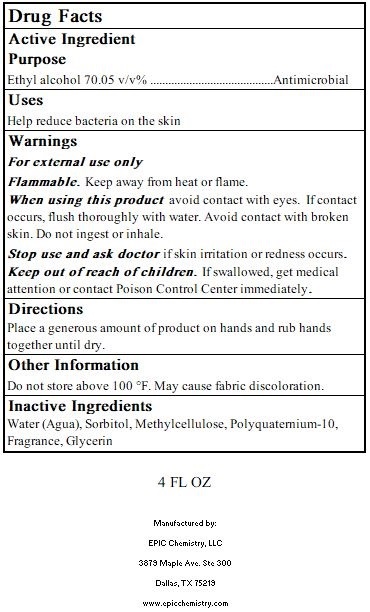 DRUG LABEL: EHS7000
NDC: 77022-1113 | Form: GEL
Manufacturer: EPIC Chemistry LLC
Category: otc | Type: HUMAN OTC DRUG LABEL
Date: 20200917

ACTIVE INGREDIENTS: ALCOHOL 70.05 1/1 1
INACTIVE INGREDIENTS: WATER 33.12 1/1 1; METHYLCELLULOSE, UNSPECIFIED 0.6 1/1 1; POLYQUATERNIUM-10 (30000 MPA.S AT 2%) 0.6 1/1 1; SORBITOL 1.13 1/1 1; GLYCERIN 0.38 1/1 1

8 OZ

Active Ingredient

Ethyl Alcohol 70.05 v/v% Antimicrobial

Uses

Help reduce bacteria on the skin

Warnings

For external use only

Flammable. Keep away from heat or flame.

When using this product avoid contact with eyes. If contact occurs, flush thoroughly with water. Avoid contact with broken skin. Do not ingest or inhale.

Stop use and ask doctor if skin irritation or redness occurs.

Keep out of reach of children. If swallowed, seek medical attention or contact Poison Control Center immediately.

Directions

Place a generous amount of product on hands and rub hands together until dry.

Other information

Do not store above 100° F. May cause fabric discoloration.

Inactive ingredients

Water (Agua), Sorbitol, Methycellulose, Polyquaternium-10, Fragrance, Glycerin

Dosage

Use a liberal amount in palm of hand.

Notice

Keep out of reach of children.

Indications & Usage

For use when soap and water are not available, or in addition to.